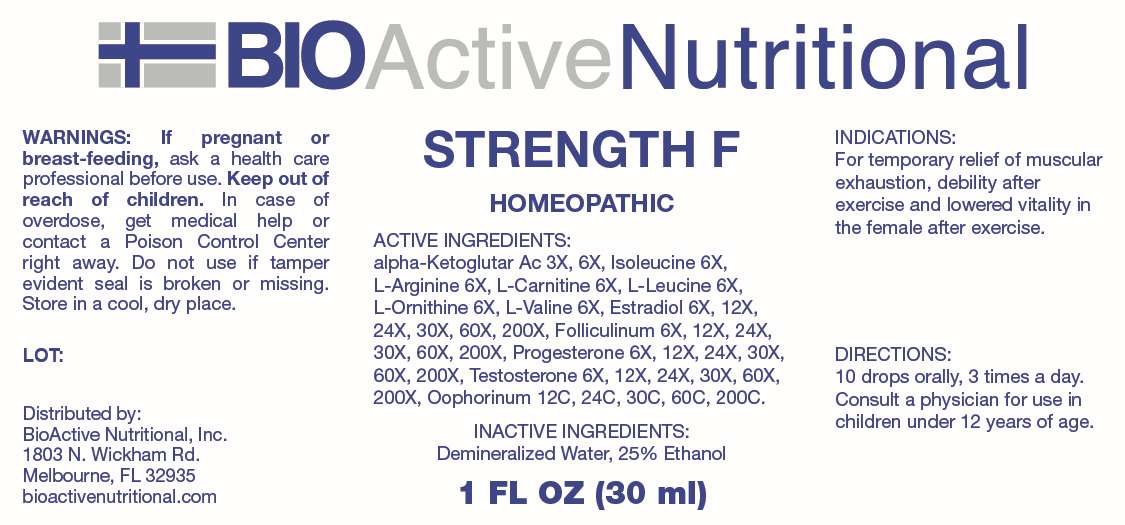 DRUG LABEL: Strength F
NDC: 43857-0650 | Form: LIQUID
Manufacturer: BioActive Nutritional, Inc.
Category: homeopathic | Type: HUMAN OTC DRUG LABEL
Date: 20250103
DEA Schedule: CIII

ACTIVE INGREDIENTS: OXOGLURIC ACID 3 [hp_X]/1 mL; ISOLEUCINE 6 [hp_X]/1 mL; ARGININE 6 [hp_X]/1 mL; LEVOCARNITINE 6 [hp_X]/1 mL; LEUCINE 6 [hp_X]/1 mL; ORNITHINE 6 [hp_X]/1 mL; VALINE 6 [hp_X]/1 mL; ESTRADIOL 6 [hp_X]/1 mL; ESTRONE 6 [hp_X]/1 mL; PROGESTERONE 6 [hp_X]/1 mL; TESTOSTERONE 6 [hp_X]/1 mL; SUS SCROFA OVARY 12 [hp_C]/1 mL
INACTIVE INGREDIENTS: WATER; ALCOHOL

DRUG FACTS:

ACTIVE INGREDIENTS:

Alpha-Ketoglutaricum Acidum 3X, 6X, Isoleucine 6X, L-Arginine 6X, L Carnitine 6X, L-Leucine 6X, L-Ornithine 6X, L-Valine 6X, Estradiol 6X, 12X, 24X, 30X, 60X, 200X, Folliculinum 6X, 12X, 24X, 30X, 30X, 200X, Progesterone 6X, 12X, 24X, 30X, 60X, 200X, Testosterone 6X, 12X, 24X, 30X, 60X, 200X, Oophorinum 12C, 24C, 30C, 60C, 200C.

PURPOSE:

For temporary relief of muscular exhaustion, debility after exercise and lowered vitality in the female after exercise.

WARNINGS:

If pregnant or breast-feeding, ask a health care professional before use.

Keep out of reach of children. In case of overdose, get medical help or contact a Poison Control Center right away.

Do not use if tamper evident seal is broken or missing.

Store in cool, dry place.

KEEP OUT OF REACH OF CHILDREN

In case of overdose, get medical help or contact a Poison Control Center right away.

DIRECTIONS:

10 drops orally, 3 times a day. Consult a physician for use in children under 12 years of age.

INDICATIONS:

For temporary relief of muscular exhaustion, debility after exercise and lowered vitality in the female after exercise.

INACTIVE INGREDIENTS:

Demineralized Water, 25% Ethanol

QUESTIONS:

Distributed by:
BioActive Nutritional, Inc.
1803 N. Wickham Rd.
Melbourne, FL 32935
bioactivenutritional.com

PACKAGE LABEL DISPLAY:

BIOActiveNutritional

STRENGTH F

HOMEOPATHIC

1 FL OZ (30 ml)